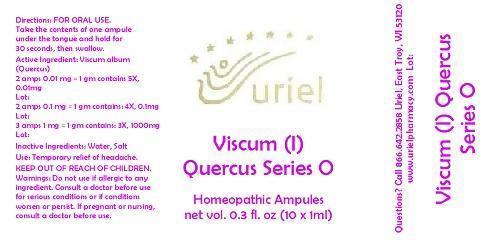 DRUG LABEL: Viscum (I) Quercus Series 0
NDC: 48951-9083 | Form: LIQUID
Manufacturer: Uriel Pharmacy Inc.
Category: homeopathic | Type: HUMAN OTC DRUG LABEL
Date: 20140825

ACTIVE INGREDIENTS: VISCUM ALBUM FRUITING TOP 3 [hp_X]/1 mL
INACTIVE INGREDIENTS: WATER; SODIUM CHLORIDE

Viscum (I) Quercus Series 0

INDICATIONS AND USAGE

Directions: FOR ORAL USE.

Inactive Ingredients: Water, Salt

PURPOSE

Use: Temporary relief of headache.

KEEP OUT OF REACH OF CHILDREN.

WARNINGS

Warnings: Do not use if allergic to any ingredient. Consult a doctor before use for serious conditions or if conditions worsen or persist. If pregnant or nursing, consult a doctor before use.

QUESTIONS

Questions? Call 866.642.2858 Uriel, East Troy, WI 53120 www.urielpharmacy.com